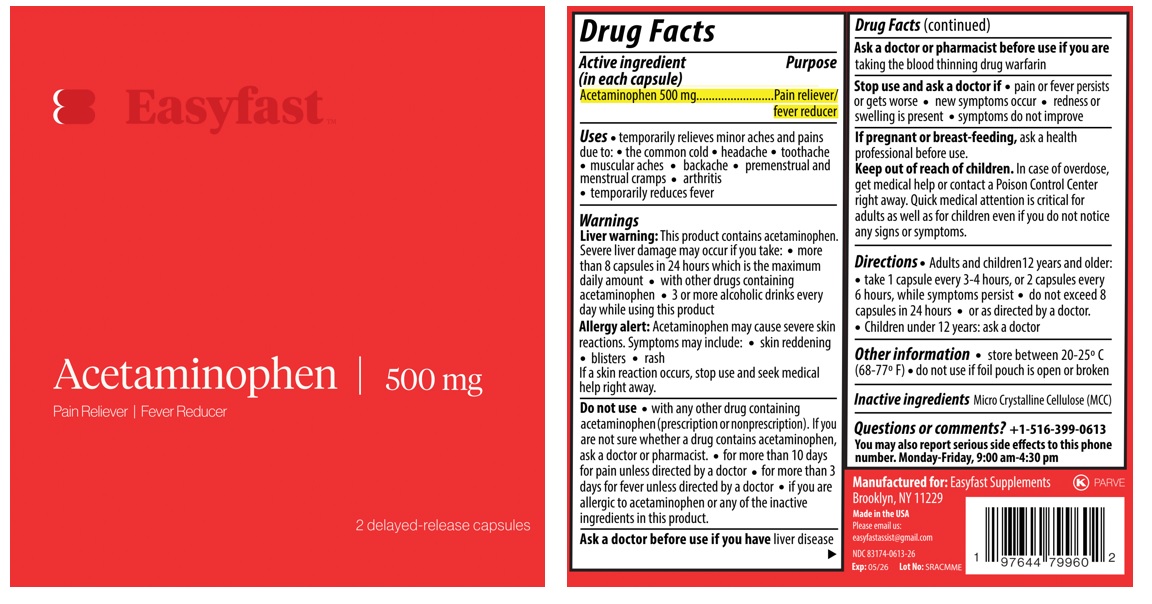 DRUG LABEL: Easyfast
NDC: 83174-613 | Form: CAPSULE
Manufacturer: Easyfast Supplements LLC
Category: otc | Type: HUMAN OTC DRUG LABEL
Date: 20241003

ACTIVE INGREDIENTS: ACETAMINOPHEN 500 mg/1 1
INACTIVE INGREDIENTS: MICROCRYSTALLINE CELLULOSE

EasyfastTM Acetaminophen

Active ingredient (in each capsule)

Acetaminophen 500 mg

Purpose

Pain reliever/fever reducer

Uses

• temporarily relieves minor aches and pains due to: • the common cold • headache • toothache • muscular aches • backache • premenstrual and menstrual cramps • arthritis
• temporarily reduces fever

Warnings

Liver warning: This product contains acetaminophen. Severe liver damage may occur if you take: • more than 8 capsules in 24 hours which is the maximum daily amount • with other drugs containing acetaminophen • 3 or more alcoholic drinks every day while using this product
Allergy alert: Acetaminophen may cause severe skin reactions. Symptoms may include: • skin reddening • blisters • rash
If a skin reaction occurs, stop use and seek medical help right away.

Do not use • with any other drug containing acetaminophen (prescription or nonprescription). If you are not sure whether a drug contains acetaminophen, ask a doctor or pharmacist. • for more than 10 days for pain unless directed by a doctor • for more than 3 days for fever unless directed by a doctor • if you are allergic to acetaminophen or any of the inactive ingredients in this product.

Ask a doctor before use if you have liver disease

Ask a doctor or pharmacist before use if you are taking the blood thinning drug warfarin

Stop use and ask a doctor if • pain or fever persists or gets worse • new symptoms occur • redness or swelling is present • symptoms do not improve

If pregnant or breast-feeding, ask a health professional before use.

Keep out of reach of children. In case of overdose, get medical help or contact a Poison Control Center right away. Quick medical attention is critical for adults as well as for children even if you do not notice any signs or symptoms.

Directions

• Adults and children12 years and older: • take 1 capsule every 3-4 hours, or 2 capsules every 6 hours, while symptoms persist • do not exceed 8 capsules in 24 hours • or as directed by a doctor.
• Children under 12 years: ask a doctor

Other information

• store between 20-25º C (68-77º F) • do not use if foil pouch is open or broken

Inactive ingredients

Micro Crystalline Cellulose (MCC)

Questions or comments?

+1-516-399-0613
You may also report serious side effects to this phone number. Monday-Friday, 9:00 am-4:30 pm

2 delayed-release capsules

Manufactured for: Easyfast Supplements
Brooklyn, NY 11229

Made in the USA

Please email us:
easyfastassist@gmail.com